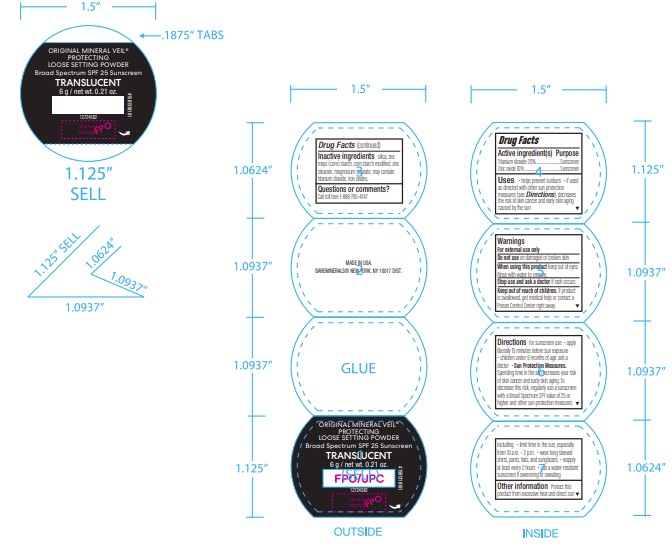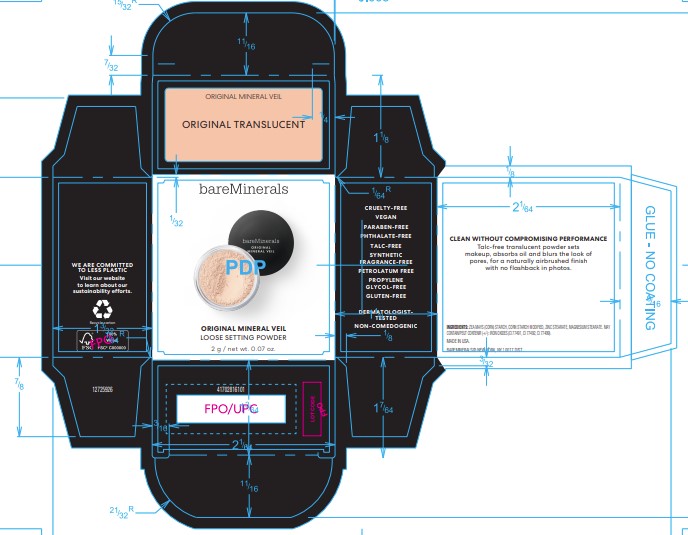 DRUG LABEL: BareMinerals
NDC: 98132-159 | Form: POWDER
Manufacturer: Orveon Global US LLC
Category: otc | Type: HUMAN OTC DRUG LABEL
Date: 20231004

ACTIVE INGREDIENTS: TITANIUM DIOXIDE 25 g/100 g; ZINC OXIDE 10 g/100 g
INACTIVE INGREDIENTS: SILICON DIOXIDE; STARCH, CORN; ZINC STEARATE; MAGNESIUM STEARATE; FERRIC OXIDE RED

bareMinerals Original Mineral Veil Protecting Loose Setting Powder SPF 25

Drug Facts

ACTIVE INGREDIENT

Active Ingredients | Purpose
Titanium Dioxide 25% | Sunscreen
Zinc Oxide 10% | Sunscreen

Uses

- Helps prevent sunburn
- Higher SPF gives more sunburn protection

Warnings

For external use only

When using this product

- Keep out of eyes
- Rinse with water to remove

Stop use and ask a doctor if

- Rash or irritation develops and lasts

- Keep out of reach of children.

If swallowed, get medical help or contact a Poison Control Center right away.

Directions

- Apply evenly before sun exposure as needed

Other Information

- Store at room temperature (59°-88°F)
- Adverse Event Reporting: 71 Stevenson St., 22 Fl., SF, CA 94105. Attn: OTC

Inactive Ingredients

Silica, Zea Mays (Corn) Starch, Corn Starch Modified, Zinc Stearate, Magnesium Stearate May Contain: Iron Oxides.

Dist. by Bare Escentuals Beauty, Inc., San Francisco, CA 94105, USA

PRINCIPAL DISPLAY PANEL - 6 g and 2 g Jar Label (Original)

bareMinerals
ORIGINAL SPF 25 Mineral Veil

original SPF 25
mineral veil

6 g / 0.21 Oz.